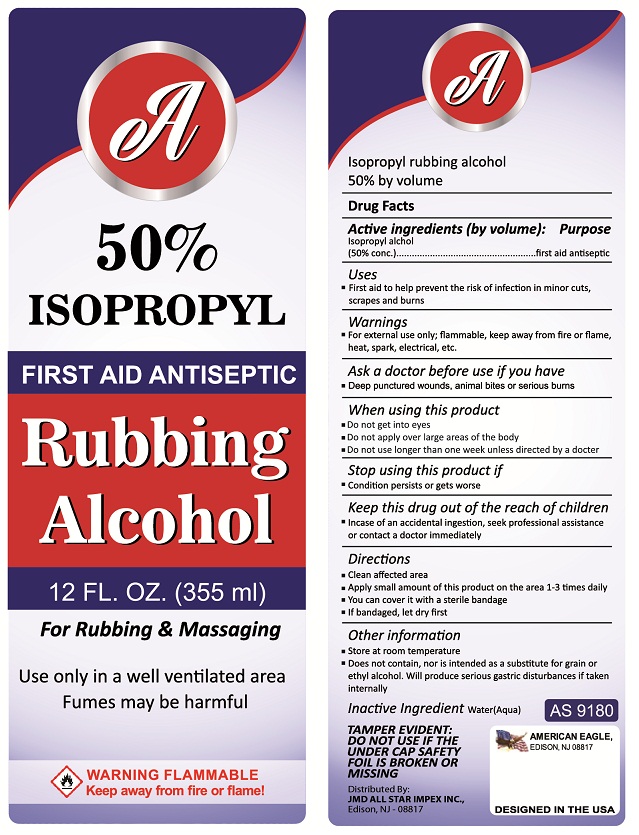 DRUG LABEL: A
NDC: 69859-003 | Form: LIQUID
Manufacturer: JT Cosmetics and Chemicals
Category: otc | Type: HUMAN OTC DRUG LABEL
Date: 20151228

ACTIVE INGREDIENTS: ISOPROPYL ALCOHOL 50 mL/100 mL
INACTIVE INGREDIENTS: WATER

A 50% ISOPROPYL Rubbing Alcohol

Active ingredients (by volume):

Isopropyl alcohol (50% conc.)

Purpose

first aid antiseptic

KEEP OUT OF REACH OF CHILDREN

Keep this drug out of the reach of children
• Incase of an accidental ingestion, seek professional assistance or contact a doctor immediately

Uses
• First aid to help prevent the risk of infection in minor cuts, scrapes and burns

Warnings
• For external use only; flammable, keep away from fire or flame, heat, spark, electrical, etc.

Ask a doctor before use if you have
• Deep punctured wounds, animal bites or serious burns

When using this product
• Do not get into eyes
• Do not apply over large areas of the body
• Do not use longer than one week unless directed by a doctor

Stop using this product if
• Condition persists or gets worse

Directions
• Clean affected area
• Apply small amount of this product on the area 1-3 times daily
• You can cover it with a sterile bandage
• If bandaged, let dry first

Inactive Ingredient Water(Aqua)

Other information
• Store at room temperature
• Does not contain, nor is intended as a substitute for grain or ethyl alcohol. Will produce serious gastric disturbances if taken internally

FIRST AID ANTISEPTIC

For Rubbing & Massaging

Use only in a well ventilated area

Fumes may be harmful

WARNING FLAMMABLE
Keep away from fire or flame!

TAMPER EVIDENT: DO NOT USE IF THE UNDER CAP SAFETY FOIL IS BROKEN OR MISSING

Distributed By:
JMD ALL STAR IMPEX INC.,
Edison, NJ - 08817

DESIGNED IN THE USA